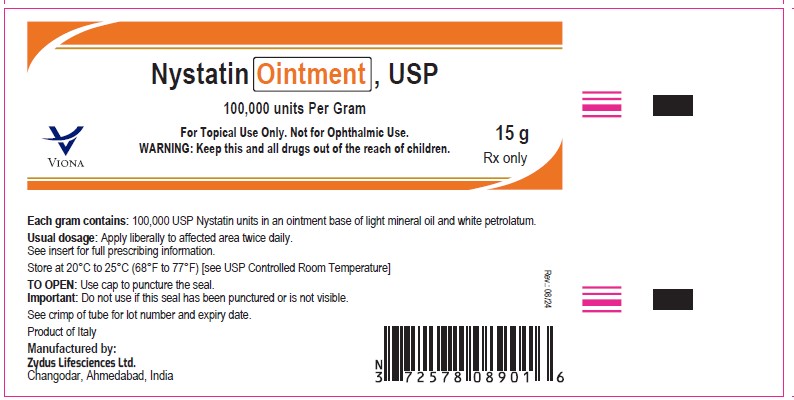 DRUG LABEL: Nystatin
NDC: 70771-1357 | Form: OINTMENT
Manufacturer: Zydus Lifesciences Limited
Category: prescription | Type: HUMAN PRESCRIPTION DRUG LABEL
Date: 20240816

ACTIVE INGREDIENTS: NYSTATIN 100000 U/1 g
INACTIVE INGREDIENTS: MINERAL OIL; PETROLATUM

Nystatin Ointment USP
For Topical Use Only
Not for Ophthalmic Use

PACKAGE LABEL.PRINCIPAL DISPLAY PANEL

NDC 70771-1357-1

Nystatin Ointment USP, 15 g

Rx only